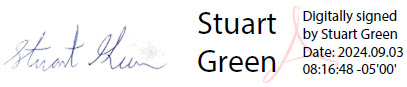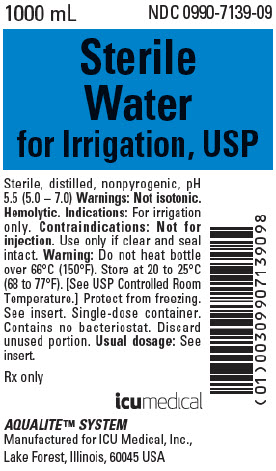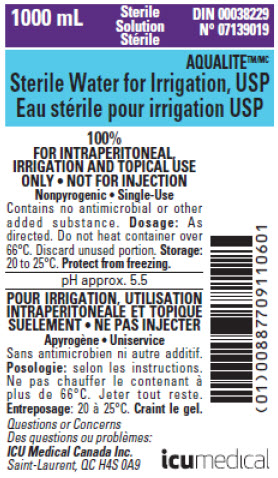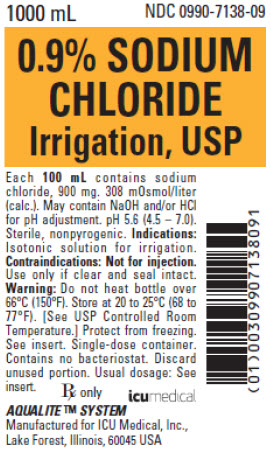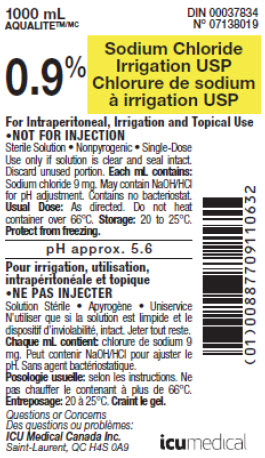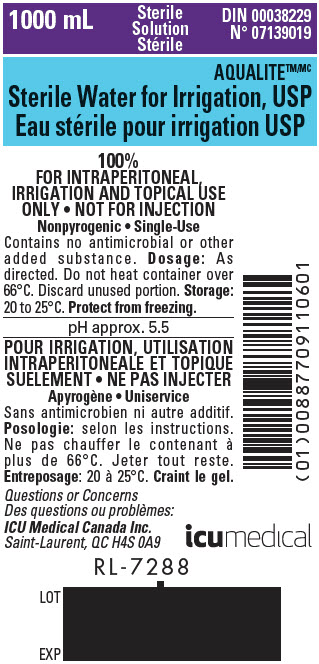 DRUG LABEL: Sterile Water
NDC: 0990-8139 | Form: IRRIGANT
Manufacturer: ICU Medical Inc.
Category: prescription | Type: HUMAN PRESCRIPTION DRUG LABEL
Date: 20251105

ACTIVE INGREDIENTS: WATER 1 mL/1 mL

Sterile Water

HEALTH CARE PROVIDER LETTER

Important Prescribing Information

September 3, 2024

Subject: Temporary distribution of Sterile water and 0.9% Sodium chloride Semi-Rigid Bottle (SRB) Irrigation with non-U.S. labeling to address drug shortages

Dear Healthcare Professional,

In order to address shortages of critical irrigation drug products, ICU Medical is coordinating with the U.S. Food and Drug Administration (FDA) to increase the availability of products from our portfolio which are manufactured and intended for the Canadian market. Temporarily and effective immediately, ICU Medical will make available for sale in the US the products listed below. These products are manufactured in the same facility and to the same specifications as ICU Medical's FDA-approved drug products; however, they are not labeled with current FDA-approved labeling. The information contained in this letter pertains only to the products listed below, which are not approved by FDA.

Product Description | Size | Canadian DIN | NDC
Sterile Water for Irrigation, USP | 1000 mL | DIN 00038229 | 0990-8139-10
0.9% Sodium Chloride Irrigation, USP | 250 mL | DIN 00037834 | 0990-5138-25
0.9% Sodium Chloride Irrigation, USP | 500 mL | DIN 00037834 | 0990-5138-50
0.9% Sodium Chloride Irrigation, USP | 1000 mL | DIN 00037834 | 0990-8138-10

There are some key differences in the labeling between the U.S. FDA-approved products and the Canadian products. Please see the product comparison tables at the end of this letter for additional information.

The barcode may not register accurately on the U.S. scanning systems. Institutions should manually input the product into their systems to confirm that barcode systems provide correct information when the product is scanned. Alternative procedures should be followed to assure that the correct drug product is being used and administered to individual patients.

The U.S. FDA-approved products are available by prescription only in the U.S. However, the Canadian products do not have the statement "Rx only" on their labeling.

Please refer to the FDA-approved package insert for the full prescribing information of each drug product.

If you have any questions about ordering SRB irrigation products, please contact ICU Medical Customer Care at (877) 946-7747 or email uscustomercare@icumed.com. For medical questions, please call ICU Medical Information at (800) 241-4002 or email Med-info_US@icumed.com.

To report adverse events or quality problems experienced with the use of this product, please call ICU Medical Global Complaint Management at (844) 654-7780 or email ProductComplaintsPP@icumed.com.

Adverse events or quality problems experienced with the use of this product may also be reported to the FDA's MedWatch Adverse Event Reporting Program either online, or regular mail, or by fax:

- Complete and submit the report Online: www.fda.gov/medwatch/report.htm
- Regular mail or Fax: Download form www.fda.gov/MedWatch/getforms.htm or call (800) 332-1088 to request a reporting form, then complete and return to the address on the pre-addressed form, or submit by fax to (800) FDA-0178 (1-800-332-0178).

Our team is working with customers to mitigate the impact of this shortage and are committed to returning to full levels of production as soon as possible.

Sincerely,

Stuart Green
Senior Director, Quality

Representative Product Labels Comparison Tables

Sterile Water for Irrigation, USP

 | US FDA Approved Product | Canadian Approved Product
Product Name | Sterile Water for Irrigation, USP | Sterile Water for Irrigation, USP
Indications | For irrigation only | For intraperitoneal, irrigation and topical use only
Active Ingredients | Sterile Water | Sterile Water
Additional Information | pH 5.5 (5.0 – 7.0) | pH approx. 5.5
Storage Conditions | Store at 20 to 25°C (68 to 77°F) [See USP Controlled Room Temperature] | 20 to 25°C
Container Type | AQUALITE™ Semi-Rigid Bottle | AQUALITE™ Semi-Rigid Bottle
Language | English | English and French
Additional Product Identifier | NDC number | DIN and product catalog number
Barcode | GS1 Primary Data Structure Includes product NDC Number | GS1 Primary Data Structure Includes Canada Manufacturer Number and unique product code

0.9% Sodium Chloride Irrigation, USP

 | US FDA Approved Product | Canadian Approved Product
Product Name | 0.9% Sodium Chloride Irrigation, USP | 0.9% Sodium Chloride Irrigation, USP
Indications | Isotonic solution for irrigation | For intraperitoneal, irrigation and topical use only
Active Ingredients | Each 100 mL contains sodium chloride, 900 mg | Each mL contains: Sodium chloride 9 mg
Additional Information | pH 5.6 (4.5 – 7.0) | pH approx. 5.6
Storage Conditions | Store at 20 to 25°C (68 to 77°F) [See USP Controlled Room Temperature] | 20 to 25°C
Container Type | AQUALITE™ Semi-Rigid Bottle | AQUALITE™ Semi-Rigid Bottle
Language | English | English and French
Additional Product Identifier | NDC number | DIN and product catalog number
Barcode | GS1 Primary Data Structure Includes product NDC Number | GS1 Primary Data Structure Includes Canada Manufacturer Number and unique product code

PRINCIPAL DISPLAY PANEL - 1000 mL Bottle Label

1000 mL

Sterile
Solution

DIN 00038229
N° 07139019

AQUALITE™
Sterile Water for Irrigation, USP

100%
FOR INTRAPERITONEAL,
IRRIGATION AND TOPICAL USE
ONLY • NOT FOR INJECTION
Nonpyrogenic • Single-Use
Contains no antimicrobial or other
added substance. Dosage: As
directed. Do not heat container over
66°C. Discard unused portion. Storage:
20 to 25°C. Protect from freezing.

pH approx. 5.5

Questions or Concerns

ICU Medical Canada Inc.
Saint-Laurent, QC H4S 0A9

RL-7288

LOT
EXP